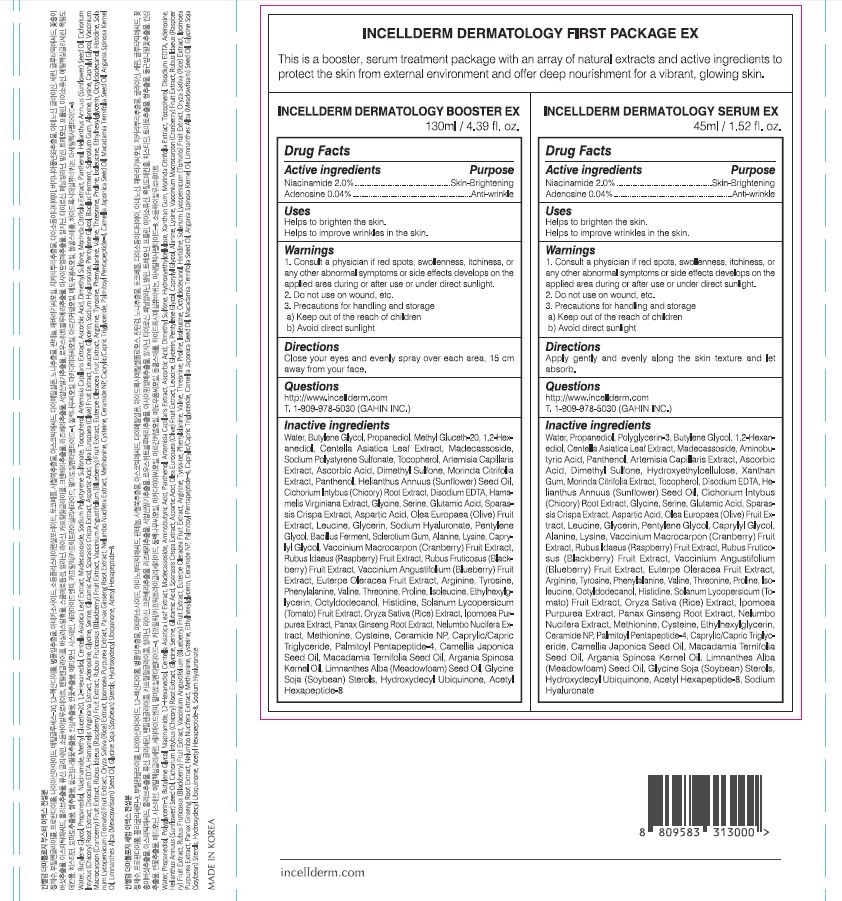 DRUG LABEL: INCELLDERM DERMATOLOGY BOOSTER EX
NDC: 72650-103 | Form: LIQUID
Manufacturer: Riman Korea Co., Ltd.
Category: otc | Type: HUMAN OTC DRUG LABEL
Date: 20210401

ACTIVE INGREDIENTS: NIACINAMIDE 2 g/100 mL; ADENOSINE 0.04 g/100 mL
INACTIVE INGREDIENTS: GLYCERIN; BUTYLENE GLYCOL

ACTIVE INGREDIENTS

Niacinamide, Adenosine

INACTIVE INGREDIENTS

Water, Butylene Glycol, Propanediol,Methyl Gluceth-20, 1,2-Hexanediol, Centella Asiatica Leaf Extract, Madecassoside, Sodium Polystyrene Sulfonate, Tocopherol, Artemisia Capillaris Extract, Ascorbic Acid, Dimethyl Sulfone, MorindaCitrifolia Extract, Panthenol, Helianthus Annuus (Sunflower) Seed Oil, Cichorium Intybus (Chicory) Root Extract, Disodium EDTA, Hamamelis Virginiana Extract, Glycine, Serine, Glutamic Acid, SparassisCrispa Extract, Aspartic Acid, Olea Europaea (Olive) Fruit Extract, Leucine, Glycerin, Sodium Hyaluronate, Pentylene Glycol, Bacillus Ferment, Sclerotium Gum, Alanine, Lysine, Caprylyl Glycol, Vaccinium Macrocarpon (Cranberry) Fruit Extract, Rubus Idaeus (Raspberry) Fruit Extract, Rubus Fruticosus (Blackberry) Fruit Extract, Vaccinium Angustifolium (Blueberry) Fruit Extract, Euterpe Oleracea Fruit Extract, Arginine, Tyrosine, Phenylalanine, Valine, Threonine, Proline, Isoleucine, Ethylhexylglycerin, Octyldodecanol, Histidine, Solanum Lycopersicum (Tomato) Fruit Extract, Oryza Sativa (Rice) Extract, Ipomoea Purpurea Extract, Panax Ginseng Root Extract, Nelumbo Nucifera Extract, Methionine, Cysteine, Ceramide NP, Caprylic/Capric Triglyceride, Palmitoyl Pentapeptide-4, Camellia Japonica Seed Oil, Macadamia Ternifolia Seed Oil, Argania Spinosa Kernel Oil, Limnanthes Alba (Meadowfoam) Seed Oil, Glycine Soja (Soybean) Sterols, Hydroxydecyl Ubiquinone, Acetyl Hexapeptide-8

PURPOSE

Helps to brighten the skin.

Helps to improve wrinkles in the skin.

WARNINGS

1. Consult a physician if red spots, swollenness, itchiness, or any other abnormal symptoms or side effects develops on the applied area during or after use or under direct sunlight.

2. Do not use on wound, etc.

3. Precautions for handling and storage

a) Keep out of the reach of children

b) Avoid direct sunlight

KEEP OUT OF REACH OF CHILDREN

Uses

Close your eyes and evenly spray over each area, 15 cm away from your face

Directions

for external use only